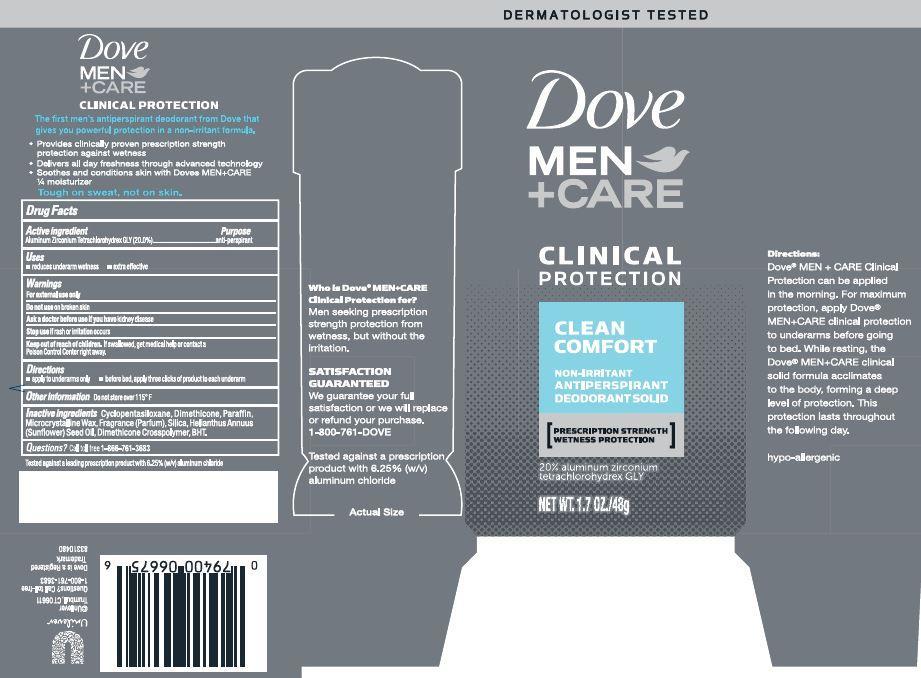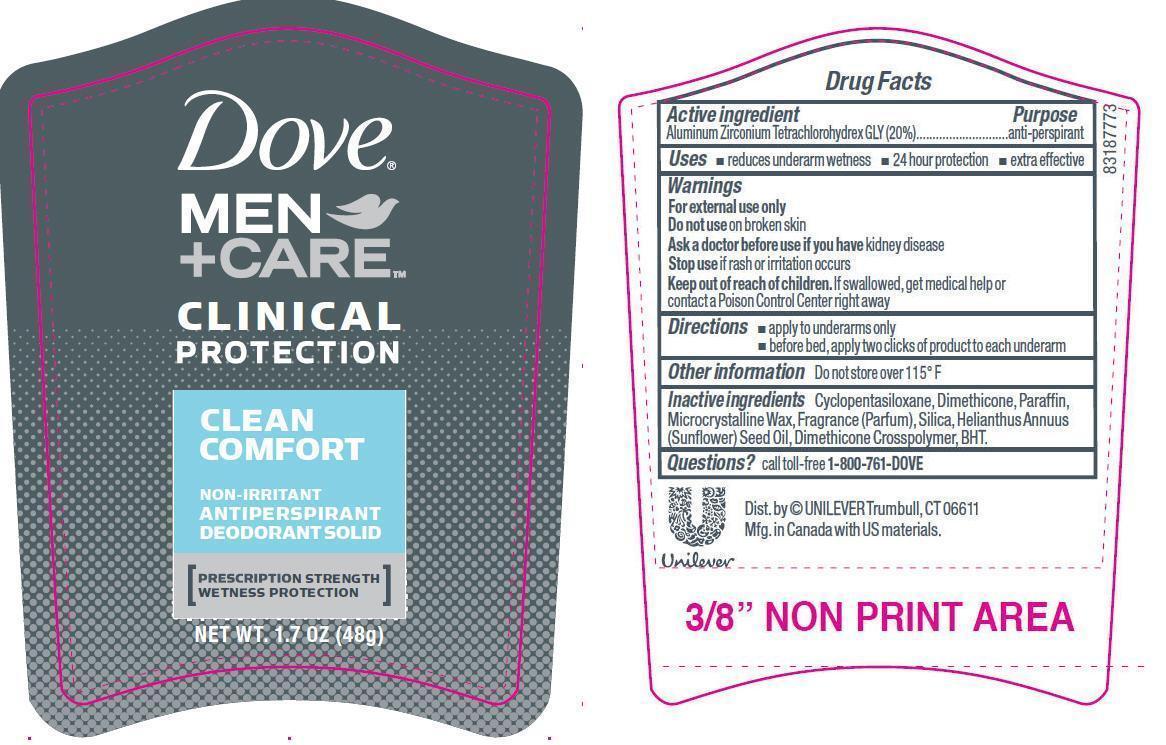 DRUG LABEL: Dove Men Clinical Protection Clean Comfort
NDC: 64942-1163 | Form: STICK
Manufacturer: Conopco Inc. d/b/a Unilever
Category: otc | Type: HUMAN OTC DRUG LABEL
Date: 20241024

ACTIVE INGREDIENTS: ALUMINUM ZIRCONIUM TETRACHLOROHYDREX GLY 20 g/100 g
INACTIVE INGREDIENTS: CYCLOMETHICONE 5; DIMETHICONE; MICROCRYSTALLINE WAX; SILICON DIOXIDE; SUNFLOWER OIL; BUTYLATED HYDROXYTOLUENE; PARAFFIN

Dove Men Clinical Protection Clean Comfort Antiperspirant deodorant

Active Ingredient

Aluminum Zirconium Tetrachlorohydrex GLY (20%)

Purpose
anti-perspirant

Uses
· reduces underarm wetness
· 24 hour protection
· extra effective

Warnings
For external use only

Do not use on broken skin

Ask a doctor before use if you have kidney disease

Stop use if rash or irritation occurs

Keep out of reach of children. If swallowed, get medical help or contact a Poison Control Center right away.

Directions
· apply to underarms only
· before bed, apply three clicks of product to each underarm

Inactive ingredients
Cyclopentasiloxane, Dimethicone, Paraffin, Microcrystalline Wax, Fragrance (Parfum), Silica, Helianthus Annuus (Sunflower) Seed Oil, Dimethicone Crosspolymer, BHT.

QUESTIONS

Questions? Call toll-free 1-800-761- 368 3